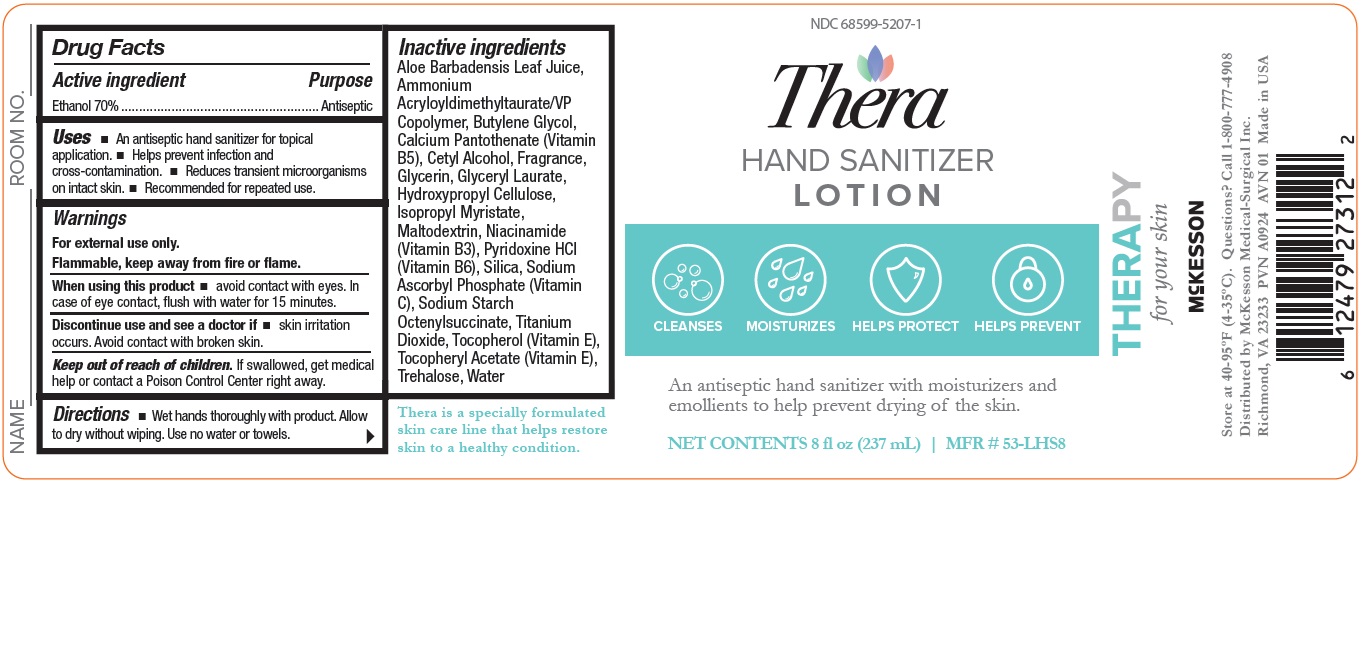 DRUG LABEL: Hand Sanitizer
NDC: 68599-5207 | Form: LOTION
Manufacturer: McKesson Medical-Surgical
Category: otc | Type: HUMAN OTC DRUG LABEL
Date: 20241121

ACTIVE INGREDIENTS: ALCOHOL 70 mL/100 mL
INACTIVE INGREDIENTS: GLYCERYL LAURATE; OCTENYLSUCCINIC ACID; WATER; SODIUM ASCORBYL PHOSPHATE; TITANIUM DIOXIDE; TOCOPHEROL; BUTYLENE GLYCOL; AMMONIUM ACRYLOYLDIMETHYLTAURATE/VP COPOLYMER; PYRIDOXINE HYDROCHLORIDE; MALTODEXTRIN; ALOE VERA LEAF; TREHALOSE; HYDROXYPROPYL CELLULOSE, UNSPECIFIED; ISOPROPYL MYRISTATE; GLYCERIN; NIACINAMIDE; CETYL ALCOHOL; SILICON DIOXIDE; .ALPHA.-TOCOPHEROL ACETATE; CALCIUM PANTOTHENATE

Hand sanitizer lotion

Drug Facts

Active Ingredient
Ethanol 70%

Purpose
Antiseptic

Uses

- An effective antimicrobial hand cleanser for topical application
- Recommended for repeated use
- Reduces transient microorganisms on intact skin
- Keeps hands from drying out due to repeated uses

Warnings

- For External Use Only
- Flammable, keep away from fire or open flame

When using this product:

- Avoid contact with eyes
- In case of eye contact, flush with water for 15 minutes
- Discontinue use and see a doctor if irritation occurs
- Avoid contact with broken skin

Keep out of reach of children.

Directions

- Wet hands thoroughly with product. Allow to dry without wiping. Use no water or

towels

Other information

- Not tested on animals

Inactive Ingredients
Aloe Barbadensis Leaf Juice, Ammonium Acryloyldimethyltaurate/VP Copolymer, Butylene
Glycol, Calcium Pantothenate (Vitamin B5), Cetyl Alcohol, Fragrance, Glycerin, Glyceryl
Laurate, Hydroxypropyl Cellulose, Isopropyl Myristate, Maltodextrin, Niacinamide
(Vitamin B3), Pyridoxine HCl (Vitamin B6), Silica, Sodium Ascorbyl Phosphate (Vitamin
C),Sodium Starch Octenylsuccinate, Titanium Dioxide, Tocopherol (Vitamin E),
Tocopheryl Acetate (Vitamin E), Trehalose, Water

Questions?
Call 1-800-777-4908

PACKAGE LABEL

68599-5207-1

Hand Sanitizer Lotion

An antiseptic hand sanitizer with moisturizers and
emollients to help prevent drying of the skin.

NET CONTENTS 8 fl oz (237 mL)

MFR # 53-LHS8